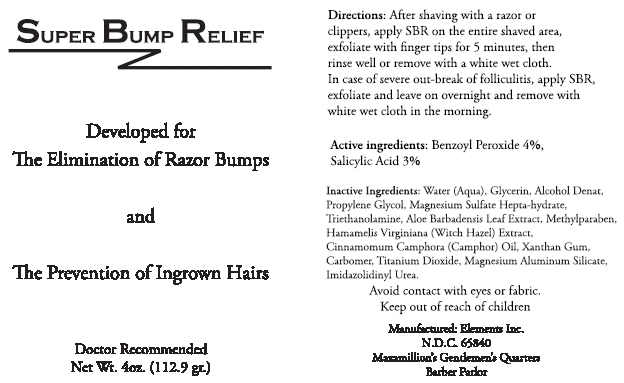 DRUG LABEL: Super Bump Relief
NDC: 65840-100 | Form: CREAM
Manufacturer: Elements Personal Care, Inc.
Category: otc | Type: HUMAN OTC DRUG LABEL
Date: 20110606

ACTIVE INGREDIENTS: BENZOYL PEROXIDE 4 g/100 g; SALICYLIC ACID 3 g/100 g
INACTIVE INGREDIENTS: WATER; ALCOHOL; PROPYLENE GLYCOL; MAGNESIUM SULFATE HEPTAHYDRATE; TROLAMINE; ALOE VERA LEAF; METHYLPARABEN; CAMPHOR OIL; XANTHAN GUM; TITANIUM DIOXIDE; MAGNESIUM ALUMINUM SILICATE; IMIDUREA

Super Bump Relief

Active ingredient

Benzoyl Peroxide 4%

Salicylic Acid 3%

Purpose

Elimination of razor bumps and prevention of ingrown hairs

Uses

Elimination of razor bumps and prevention of ingrown hairs

Warnings

Avoid contact with eyes or fabric.

Keep out of reach of children.

Directions

After shaving with a razor or clippers, apply SBR on the entire shaved area, exfoliate with finger tips for 5 minutes, then rinse well or remove with a white wet cloth. In case of severe out-break of folliculitis, apply SBR, exfoliate and leave on overnight and remove with white wet cloth in the morning.

Inactive ingredients

Water (Aqua), Glycerin, Alcohol Denat, Propylene Glycol, Magnesium Sulfate Hepta-hydrate, Triethanolamine, Aloe Barbadensis Leaf Extract, Methylparaben, Hamamelis Virginiana (Witch Hazel) Extract, Cinnamomum Camphora (Camphor) Oil, Xanthan Gum, Carbomer, Titanium Dioxide, Magnesium Aluminum Silicate, Imidazolidinyl Urea.

Package/Label Principal Display Panel - Bottle Label

Bottle Label

Super Bump Relief

Developed for

The Elimination of Razor Bumps

and

The Prevention of Ingrown Hairs

Doctor Recommended

Net Wt. 4 oz. (112.9 gr.)

Manufactured: Elements Inc.

N.D.C. 65840

Maxamillion's Gentlemen's Quarters

Barber Parlor